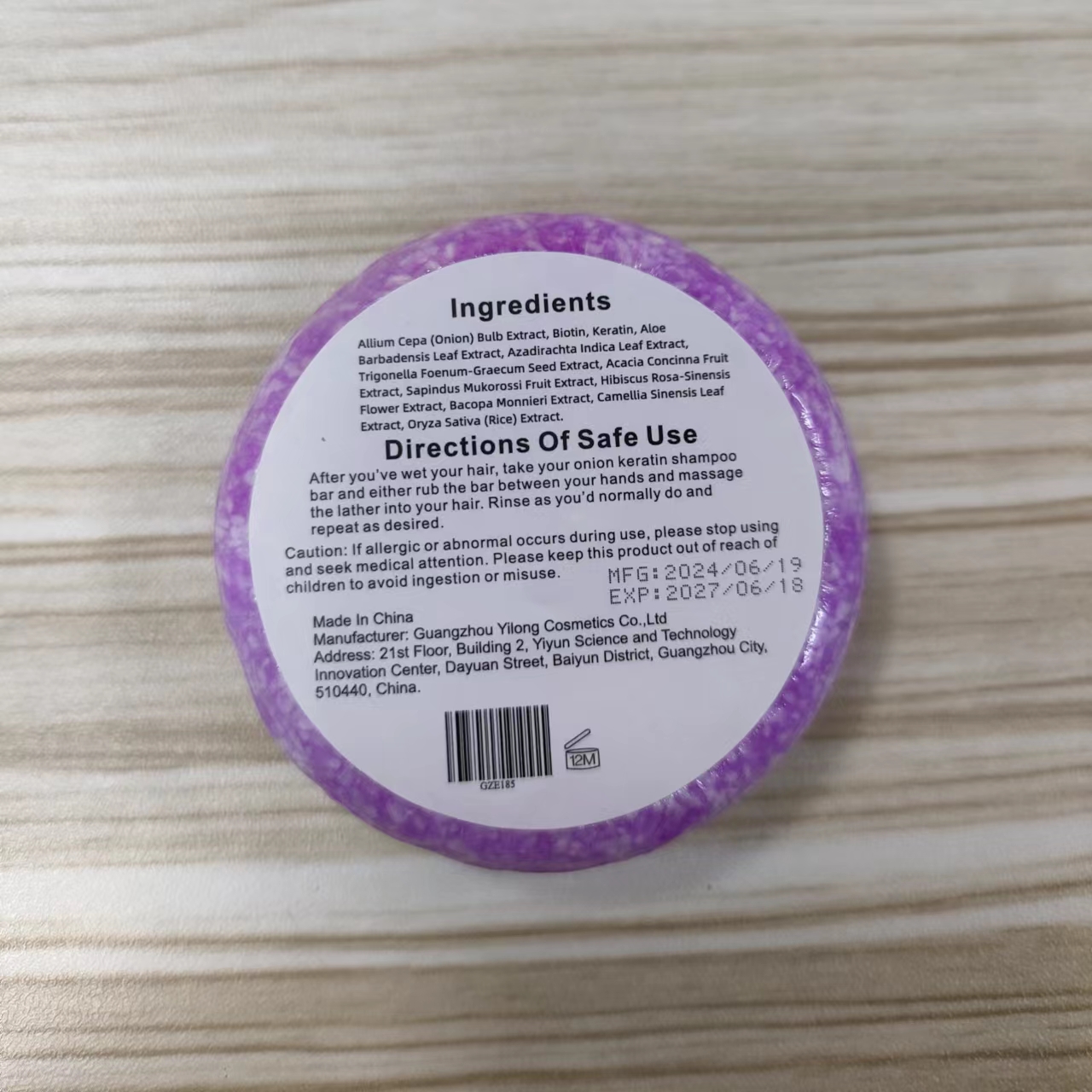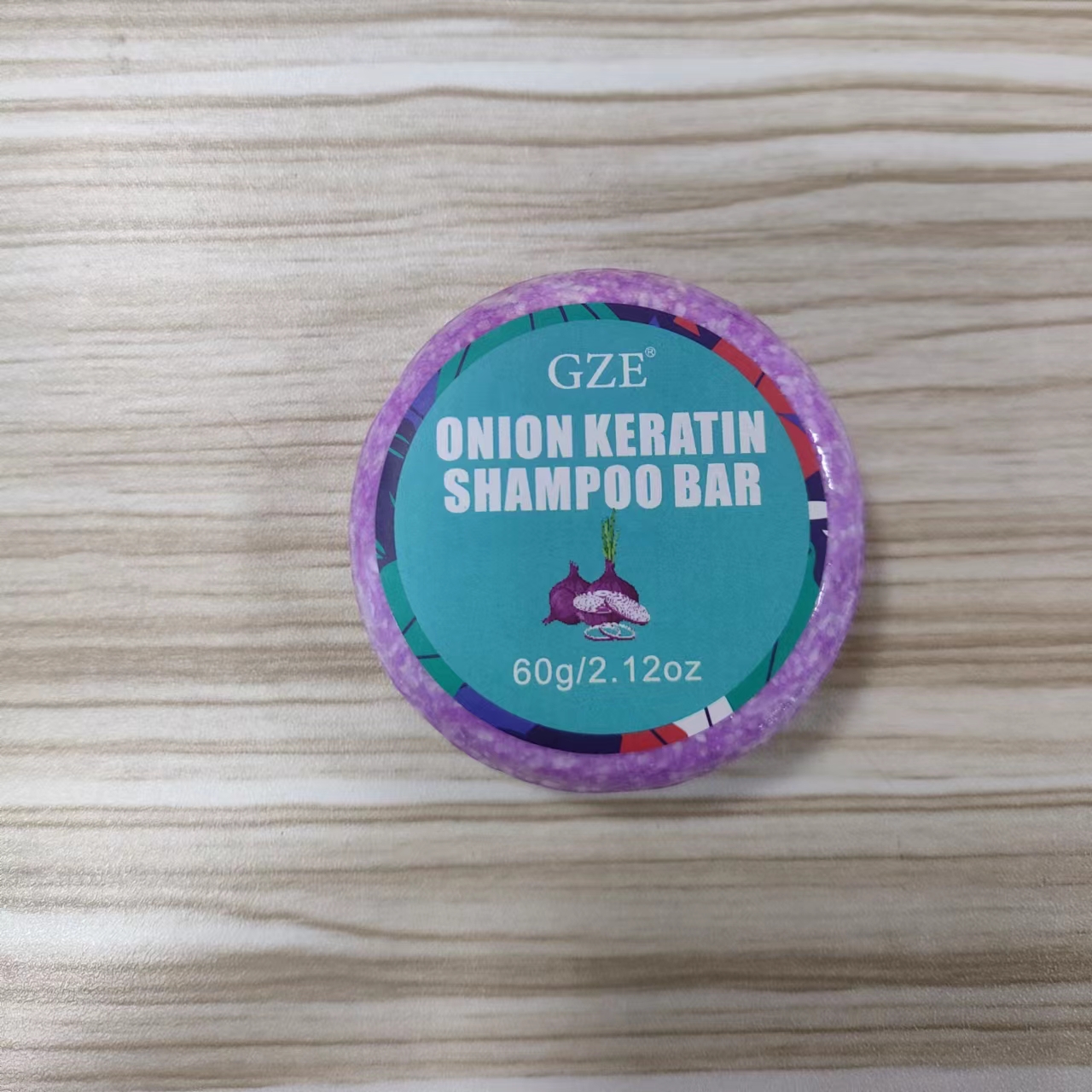 DRUG LABEL: GZE Onion Keratin ShampooBar
NDC: 83566-185 | Form: SOAP
Manufacturer: Guangzhou Yilong Cosmetics Co., Ltd
Category: otc | Type: HUMAN OTC DRUG LABEL
Date: 20240720

ACTIVE INGREDIENTS: HAIR KERATIN AMINO ACIDS 10 g/100 g; BIOTIN 10 g/100 g
INACTIVE INGREDIENTS: BACOPA MONNIERI WHOLE; HIBISCUS ROSA-SINENSIS FLOWER; AZADIRACHTA INDICA LEAF; SAPINDUS MUKOROSSI FRUIT; TRIGONELLA FOENUM-GRAECUM WHOLE; ONION; ALOE ANDONGENSIS LEAF; ACACIA CONCINNA FRUIT; CAMELLIA SINENSIS FLOWER; ORYZA SATIVA WHOLE

GZE Onion Keratin ShampooBar

ACTIVE INGREDIENT

Biotin

Keratin

INACTIVE INGREDIENT

Allium Cepa (Onion) Bulb Extract

Aloe Barbadensis Leaf Extract

Azadirachta Indica Leaf Extract

Trigonella Foenum-Graecum Seed Extract

Acacia Concinna Fruit Extract

Sapindus Mukorossi Fruit Extract

Hibiscus Rosa-Sinensis Flower Extract

Bacopa Monnieri Extract

Camellia Sinensis Leaf Extract

Oryza Sativa (Rice) Extract

PURPOSE

hair care

INDICATIONS AND USAGE

After you've wet your hair, take your onion kerntin shampoo bar and either rub the bar between your hands and massag the lather into your hair, Rinse as you'd normally do and repeat as desired.

WARNINGS

For external use only.

Stop use and ask a doctor if rash occurs.

Do not use on damaged or broken skin.

When using this product keep out of eyes. Rinse with water to remove.

Keep out of reach of children. If swallowed, get medical help or contact a Poison Control Center right away.

DOSAGE AND ADMINISTRATION

After you've wet your hair, take your onion kerntin shampoo bar and either rub the bar between your hands and massag the lather into your hair, Rinse as you'd normally do and repeat as desired.